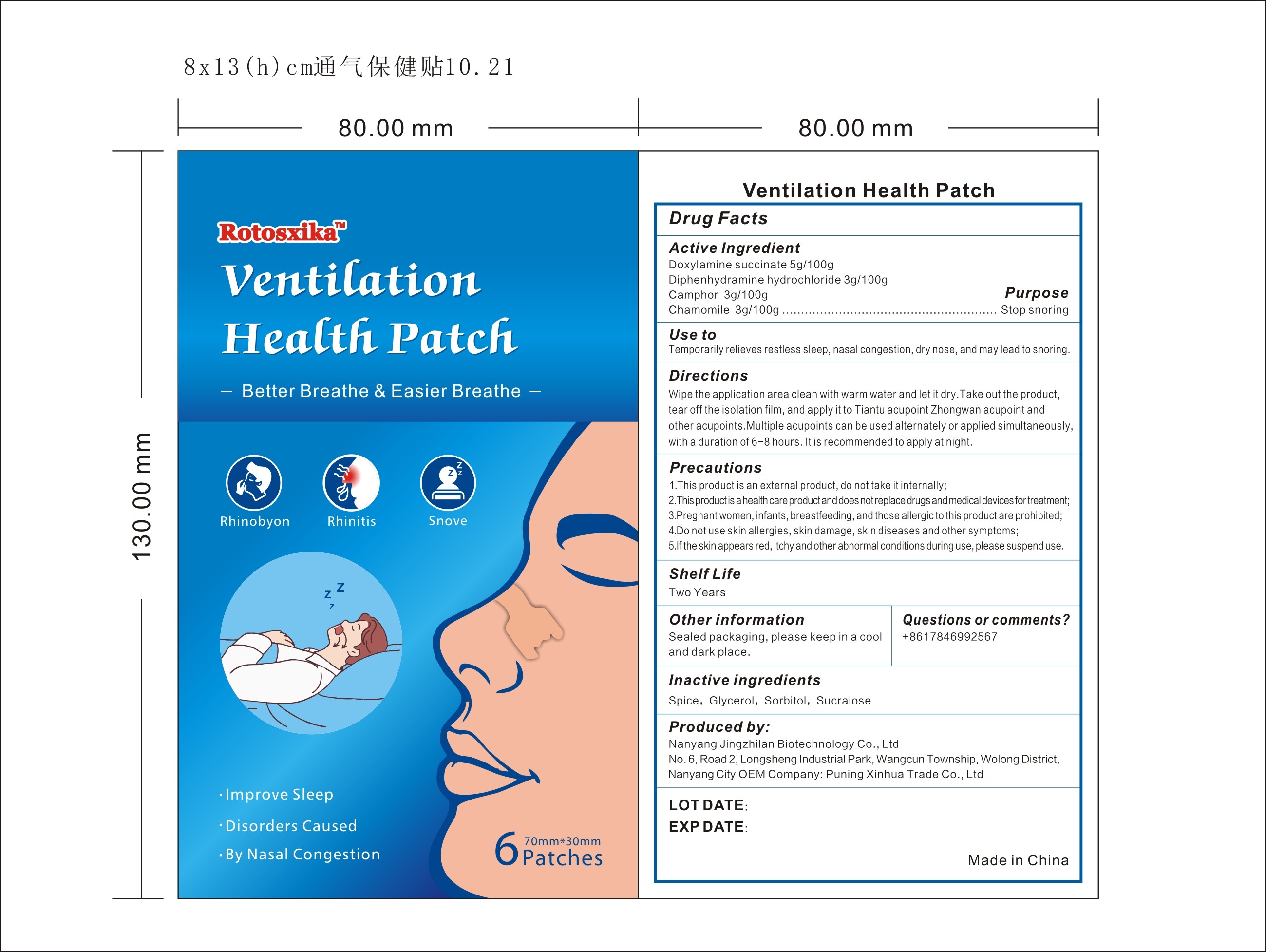 DRUG LABEL: Rotosxika Ventilation Health patch
NDC: 83702-021 | Form: PATCH
Manufacturer: Puning Xinhua Trade Co., Ltd.
Category: otc | Type: HUMAN OTC DRUG LABEL
Date: 20231019

ACTIVE INGREDIENTS: DIPHENHYDRAMINE HYDROCHLORIDE 3 g/100 g; DOXYLAMINE SUCCINATE 5 g/100 g; CHAMOMILE 3 g/100 g; CAMPHOR (NATURAL) 3 g/100 g
INACTIVE INGREDIENTS: SORBITOL; ALLSPICE; GLYCEROL FORMAL; SUCRALOSE

Rotosxika Ventilation Health patch-83702-021-12

Active ingredient: Doxylamine succinate 5g/100g, Diphenhydramine hydrochloride 3g/100g, Camphor 3g/100g, Chamomile 3g/100g

Purpose: Helps sleep

INDICATIONS AND USAGE

Use to: Temporarily relieves restless sleep, nasal congestion, dry nose, and may lead to snoring.

DOSAGE AND ADMINISTRATION

Directions: Wipe the application area clean with warm water and let it dry.Take out the product, tear off the isolation film, and apply it to Tiantu acupoint Zhongwan acupoint and other acupoints.Multiple acupoints can be used alternately or applied simultaneously, with a duration of 6-8 hours. It is recommended to apply at night.

WARNINGS

Precautions:
1.This product is an external product, do not take it internally;

2.This product is a health care product and does not replace drugs and medical devices fortreatment;

3.Pregnant women, infants, breastfeeding, and those allergic to this product are prohibited;

4.Do not use skin allergies, skin damage, skin diseases and other symptoms;

5.If the skin appears red, itchy and other abnormal conditions during use, please suspend use.

Questions or comments? +8617846992567

Inactive Ingredients: Spice,Glycerol,Sorbitol,Sucralose

Other information: Sealed packaging,please keep in a cool and dark place.

Produced by:
Nanyang Jingzhilan Biotechnology Co., Ltd
No.6,Road2,Longsheng Industrial Park,Wangcun Township, Wolong District, Nanyang City
OEM Company: Puning Xinhua Trade Co., Ltd

Made in China

KEEP OUT OF REACH OF CHILDREN

Same as WARNINGS SECTION

Label